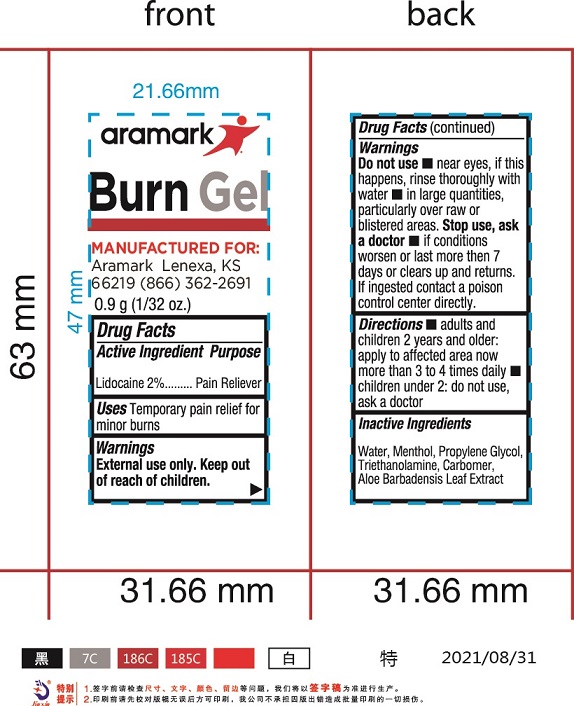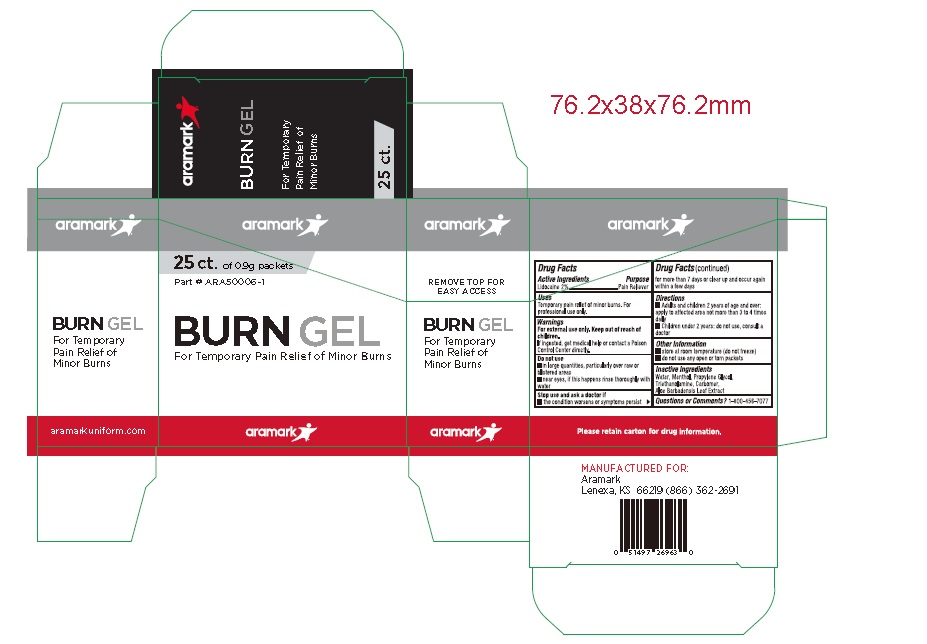 DRUG LABEL: Aramark Star Burn Gel
NDC: 81238-4600 | Form: GEL
Manufacturer: Western First Aid Safety DBA Aramark
Category: otc | Type: HUMAN OTC DRUG LABEL
Date: 20211028

ACTIVE INGREDIENTS: LIDOCAINE 20 mg/1 g
INACTIVE INGREDIENTS: WATER; MENTHOL; PROPYLENE GLYCOL; TROLAMINE; CARBOMER HOMOPOLYMER, UNSPECIFIED TYPE; ALOE VERA LEAF

Aramark Star Burn Gel

Drug Facts

Active Ingredients

Lidocaine 2.0%

Purpose

Pain reliever.

Uses

Temporary pain relief for minor burns. For

professional use only.

Warnings

For external use only.

Keep out of reach of children.

If ingested, get medical help or contact a Poison Control Center directly.

Do not use

- in large quantities, particularly over raw or blistered areas
- near eyes, if this happens rinse thoroughly with water

Stop use and ask a doctor if

• the condition worsens or symptoms persist for more

than 7 days or clear up and occur again within a few days

Directions

• Adults and children 2 years of age and older:

apply to affected area not more than 3 to 4 times daily

• Children under 2 years: do not use, consult a doctor

Other Information

• store at room temperature (do not freeze)

• do not use any open or torn packets

Inactive ingredients

Water, Menthol, Propylene Glycol,

Triethanolamine, Carbomer,

Aloe Barbadensis Leaf Extract

Questions od Comments?

1-800-456-7077

Package Labeling

aramark

25 ct. of 0.9g packets

BURN GEL

For Temporary Pain Relief of Minor Burns

aramarkuniform.com

MANUFACTURED FOR:
Aramark
Lenexa, KS 66219 886-362-2691

Please retain carton for drug information.

res